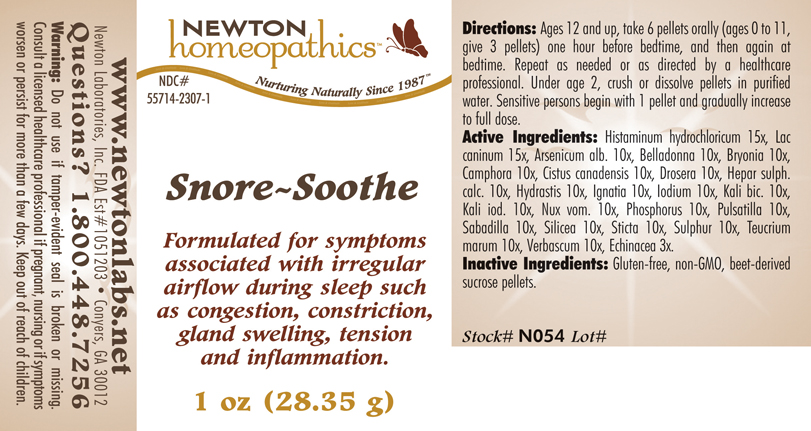 DRUG LABEL: Snore Soothe 
NDC: 55714-2307 | Form: PELLET
Manufacturer: Newton Laboratories, Inc.
Category: homeopathic | Type: HUMAN OTC DRUG LABEL
Date: 20110301

ACTIVE INGREDIENTS: Histamine Dihydrochloride 15 [hp_X]/1 g; Canis Lupus Familiaris Milk 15 [hp_X]/1 g; Arsenic Trioxide 10 [hp_X]/1 g; Atropa Belladonna 10 [hp_X]/1 g; Bryonia Alba Root 10 [hp_X]/1 g; Camphor (natural) 10 [hp_X]/1 g; Helianthemum Canadense 10 [hp_X]/1 g; Drosera Rotundifolia Flowering Top 10 [hp_X]/1 g; Calcium Sulfide 10 [hp_X]/1 g; Goldenseal 10 [hp_X]/1 g; Strychnos Ignatii Seed 10 [hp_X]/1 g; Iodine 10 [hp_X]/1 g; Potassium Dichromate 10 [hp_X]/1 g; Potassium Iodide 10 [hp_X]/1 g; Strychnos Nux-vomica Seed 10 [hp_X]/1 g; Phosphorus 10 [hp_X]/1 g; Pulsatilla Vulgaris 10 [hp_X]/1 g; Schoenocaulon Officinale Seed 10 [hp_X]/1 g; Silicon Dioxide 10 [hp_X]/1 g; Lobaria Pulmonaria 10 [hp_X]/1 g; Sulfur 10 [hp_X]/1 g; Teucrium Marum 10 [hp_X]/1 g; Verbascum Thapsus 10 [hp_X]/1 g; Echinacea, Unspecified 3 [hp_X]/1 g
INACTIVE INGREDIENTS: Sucrose

Snore - Soothe

INDICATIONS & USAGE SECTION

Snore - Soothe Formulated for symptoms associated with irregular airflow during sleep such as congestion, constriction, gland swelling, tension and inflammation.

DOSAGE & ADMINISTRATION SECTION

Ages 12 and up, take 6 pellets orally (ages 0 to 11, give 3 pellets) one hour before bedtime, and then again at bedtime. Repeat as needed or as directed by a healthcare professional. Under age 2, crush or dissolve pellets in purified water. Sensitive persons begin with 1 pellet and gradually increase to full dose.

OTC - ACTIVE INGREDIENT SECTION

Histaminum hydrochloricum 15x, Lac caninum 15x, Arsenicum alb. 10x, Belladonna 10x, Bryonia 10x, Camphora 10x, Cistus canadensis 10x, Drosera 10x, Hepar sulph.calc. 10x, Hydrastis 10x, Ignatia 10x, Iodium 10x, Kali bic. 10x, Kali iod. 10x, Nux vom. 10x, Phosphorus 10x, Pulsatilla 10x, Sabadilla 10x, Silicea 10x, Sticta 10x, Sulphur 10x, Teucrium marum 10x, Verbascum 10x, Echinacea 3x.

OTC - PURPOSE SECTION

Formulated for symptoms associated with irregular airflow during sleep such as congestion, constriction, gland swelling, tension and inflammation.

INACTIVE INGREDIENT SECTION

Inactive Ingredients: Gluten-free, non-GMO, beet-derived sucrose pellets.

QUESTIONS SECTION

www.newtonlabs.net Newton Laboratories, Inc. FDA Est # 1051203 - Conyers, GA 30012
Questions? 1.800.448.7256

WARNINGS SECTION

Warning: Do not use if tamper - evident seal is broken or missing. Consult a licensed healthcare professional if pregnant, nursing or if symptoms worsen or persist for more than a few days. Keep out of reach of children.

OTC - PREGNANCY OR BREAST FEEDING SECTION

Consult a licensed healthcare professional if pregnant, nursing or if symptoms worsen or persist for more than a few days.

OTC - KEEP OUT OF REACH OF CHILDREN SECTION

Keep out of reach of children.